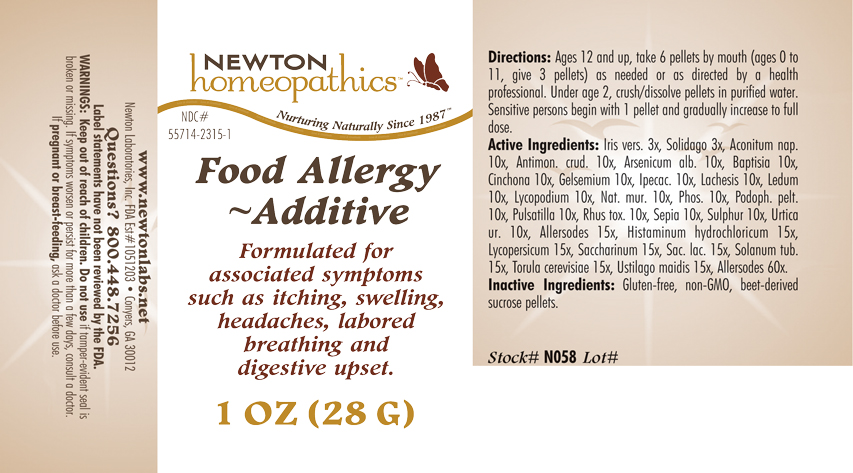 DRUG LABEL: Food Allergy - Additive 
NDC: 55714-2315 | Form: PELLET
Manufacturer: Newton Laboratories, Inc.
Category: homeopathic | Type: HUMAN OTC DRUG LABEL
Date: 20110301

ACTIVE INGREDIENTS: Egg 60 [hp_X]/1 g; Fd&c Yellow No. 5 60 [hp_X]/1 g; D&c Yellow No. 10 60 [hp_X]/1 g; Fd&c Yellow No. 6 60 [hp_X]/1 g; Carmoisine 60 [hp_X]/1 g; Amaranth 60 [hp_X]/1 g; Ponceau 4r 60 [hp_X]/1 g; Fd&c Red No. 3 60 [hp_X]/1 g; Acid Red 1 60 [hp_X]/1 g; Fd&c Blue No. 2 60 [hp_X]/1 g; Sodium Copper Chlorophyllin 60 [hp_X]/1 g; Acid Green 50 60 [hp_X]/1 g; Sodium Benzoate 60 [hp_X]/1 g; Potassium Benzoate 60 [hp_X]/1 g; Propylparaben 60 [hp_X]/1 g; Sodium Dithionate 60 [hp_X]/1 g; 2-phenylphenol 60 [hp_X]/1 g; Sodium Nitrite 60 [hp_X]/1 g; Ascorbic Acid 60 [hp_X]/1 g; Sodium Tripolyphosphate 60 [hp_X]/1 g; Aspartame 60 [hp_X]/1 g; Monosodium Glutamate 60 [hp_X]/1 g; Beef 60 [hp_X]/1 g; Pork 60 [hp_X]/1 g; Lamb 60 [hp_X]/1 g; Chicken 60 [hp_X]/1 g; Turkey 60 [hp_X]/1 g; Quahog, Unspecified 60 [hp_X]/1 g; Crab Leg, Unspecified 60 [hp_X]/1 g; Oyster, Unspecified 60 [hp_X]/1 g; Shrimp, Unspecified 60 [hp_X]/1 g; Scallop, Unspecified 60 [hp_X]/1 g; Amanita Muscaria Fruiting Body 15 [hp_X]/1 g; Onion 15 [hp_X]/1 g; Garlic 15 [hp_X]/1 g; Anacardium Occidentale Fruit 15 [hp_X]/1 g; Lycoperdon Utriforme Fruiting Body 15 [hp_X]/1 g; Caffeine 15 [hp_X]/1 g; Capsicum 15 [hp_X]/1 g; Cinnamon 15 [hp_X]/1 g; Cynara Scolymus Leaf 15 [hp_X]/1 g; Alpine Strawberry 15 [hp_X]/1 g; Abrus Precatorius Seed 15 [hp_X]/1 g; Glycyrrhiza Glabra 15 [hp_X]/1 g; Mentha Piperita 15 [hp_X]/1 g; Nutmeg 15 [hp_X]/1 g; Lactose 15 [hp_X]/1 g; Black Mustard Seed 15 [hp_X]/1 g; Solanum Nigrum Whole 15 [hp_X]/1 g; Allylthiourea 15 [hp_X]/1 g; Ustilago Maydis 15 [hp_X]/1 g; Ginger 15 [hp_X]/1 g; Brazil Nut 15 [hp_X]/1 g; Hazelnut, Unspecified 15 [hp_X]/1 g; Peanut 15 [hp_X]/1 g; Trout, Unspecified 15 [hp_X]/1 g; Cod, Unspecified 15 [hp_X]/1 g; Tuna, Unspecified 15 [hp_X]/1 g; Salmon, Unspecified 15 [hp_X]/1 g; Herring, Unspecified 15 [hp_X]/1 g; Histamine Dihydrochloride 15 [hp_X]/1 g; Solanum Lycopersicum 15 [hp_X]/1 g; Saccharin 15 [hp_X]/1 g; Solanum Tuberosum 15 [hp_X]/1 g; Saccharomyces Cerevisiae 15 [hp_X]/1 g; Aconitum Napellus 10 [hp_X]/1 g; Antimony Trisulfide 10 [hp_X]/1 g; Arsenic Trioxide 10 [hp_X]/1 g; Baptisia Tinctoria Root 10 [hp_X]/1 g; Cinchona Officinalis Bark 10 [hp_X]/1 g; Gelsemium Sempervirens Root 10 [hp_X]/1 g; Ipecac 10 [hp_X]/1 g; Lachesis Muta Venom 10 [hp_X]/1 g; Ledum Palustre Twig 10 [hp_X]/1 g; Lycopodium Clavatum Spore 10 [hp_X]/1 g; Sodium Chloride 10 [hp_X]/1 g; Phosphorus 10 [hp_X]/1 g; Podophyllum 10 [hp_X]/1 g; Pulsatilla Vulgaris 10 [hp_X]/1 g; Toxicodendron Pubescens Leaf 10 [hp_X]/1 g; Sepia Officinalis Juice 10 [hp_X]/1 g; Sulfur 10 [hp_X]/1 g; Urtica Urens 10 [hp_X]/1 g; Iris Versicolor Root 3 [hp_X]/1 g; Solidago Virgaurea Flowering Top 3 [hp_X]/1 g
INACTIVE INGREDIENTS: Sucrose

Food Allergy - Additive

INDICATIONS & USAGE SECTION

Formulated for associated symptoms such as itching, swelling, headaches, labored breathing and digestive upset.

DOSAGE & ADMINISTRATION SECTION

Directions: Ages 12 and up, take 6 pellets by mouth (ages 0 to 11, give 3 pellets) as needed or as directed by a health professional. Under age 2, crush/dissolve pellets in purified water. Sensitive persons begin with 1 pellet and gradually increase to full dose.

OTC - ACTIVE INGREDIENT SECTION

Allersodes 60x, Allersodes 15x,Histaminum hydrochloricum 15x, Lycopersicum 15x, Saccharinum 15x, Sac. lac. 15x, Solanum tub. 15x, Torula cerevisiae 15x, Ustilago maidis 15x, Aconitum nap. 10x, Antimon.crud. 10x, Arsenicum alb. 10x, Baptisia 10x, Cinchona 10x, Gelsemium 10x, Ipecac. 10x, Lachesis 10x, Ledum 10x, Lycopodium 10x, Nat. mur. 10x, Phos. 10x, Podoph. pelt. 10x, Pulsatilla 10x, Rhus tox. 10x, Sepia 10x, Sulphur 10x, Urtica ur. 10x, Iris vers. 3x, Solidago 3x.

OTC - PURPOSE SECTION

Formulated for associated symptoms such as itching, swelling, headaches, labored breathing and digestive upset.

INACTIVE INGREDIENT SECTION

Inactive Ingredients: Gluten-free, non-GMO, beet-derived sucrose pellets.

QUESTIONS SECTION

www.newtonlabs.net Newton Laboratories, Inc. FDA Est # 1051203 - Conyers, GA 30012
Questions? 1.800.448.7256

WARNINGS SECTION

Warning: Keep out of reach of children. Do not use if tamper-evident seal is broken or missing. If symptoms worsen or persist for more than a few days, consult a doctor. If pregnant or breast-feeding, ask a doctor before use.

OTC - PREGNANCY OR BREAST FEEDING SECTION

If pregnant or breast-feeding, ask a doctor before use.

OTC - KEEP OUT OF REACH OF CHILDREN SECTION

Keep out of reach of children.